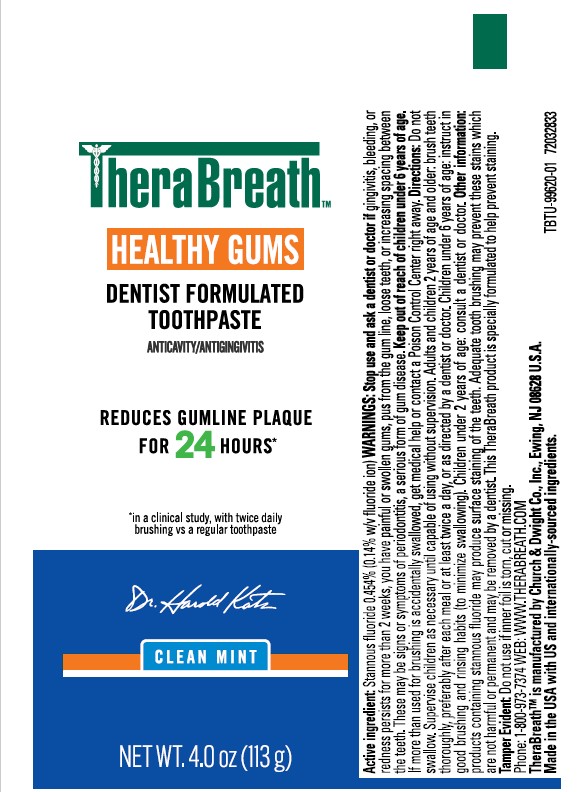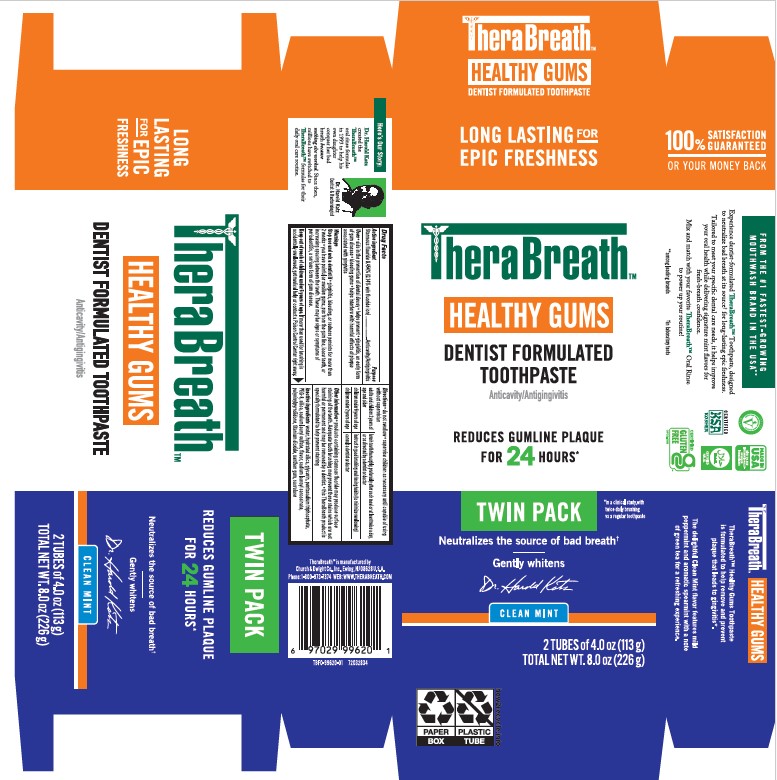 DRUG LABEL: Therabreath
NDC: 10237-271 | Form: PASTE, DENTIFRICE
Manufacturer: Church & Dwight Co., Inc.
Category: otc | Type: HUMAN OTC DRUG LABEL
Date: 20250801

ACTIVE INGREDIENTS: STANNOUS FLUORIDE 0.454 g/100 g
INACTIVE INGREDIENTS: PEG-8; SODIUM LAUROYL SARCOSINATE; SILICON DIOXIDE; PENTASODIUM TRIPHOSPHATE; HYDRATED SILICA; XANTHAN GUM; SODIUM LAURYL SULFATE; CROSPOVIDONE, UNSPECIFIED; WATER; GLYCERIN; SUCRALOSE; TITANIUM DIOXIDE

Therabreath™ Healthy Gums Dentist Formulated Toothpaste, Clean Mint

Drug Facts

Active Ingredient

Stannous fluoride 0.454% (0.14% w/v fluoride ion)

Purpose

Anticavity/Antigingivitis

Uses

• aids in the prevention of dental decay • helps prevent • gingivitis, an early form of gum disease • bleeding gums • helps interfere with harmful effects of plaque associated with gingivitis

Warnings

Stop use and ask a dentist if

• gingivitis, bleeding, or redness persists for more than 2 weeks • you have painful or swollen gums, pus from the gum line, loose teeth, or increasing spacing between the teeth. These may be signs or symptoms of periodontitis, a serious form of gum disease.

Keep out of reach of children under 6 years of age.

If more than used for brushing is accidentally swallowed, get medical help or contact a Poison Control Center right away.

Directions

• do not swallow • supervise children as necessary until capable of using without supervision

adults and children 2 years of age and older | brush teeth thoroughly, preferably after each meal or at least twice a day, or as directed by a dentist or doctor
children under 6 years of age | instruct in good brushing and rinsing habits (to minimize swallowing)
children under 2 years of age | consult a dentist or doctor

Inactive Ingredients

water, hydrated silica, glycerin, pentasodium triphosphate, PEG-8, silica, sodium lauryl sulfate, flavor, sodium lauroyl sarcosinate, polyvinylpyrrolidone, titanium dioxide, xanthan gum, sucralose

Questions or Comments?

Therabreath is manufactured by

Church & Dwight Co., Inc., Ewing, NJ 08628 U.S.A

Phone: 1-800-973-7374 WEB: WWW.THERABREATH.COM

PACKAGE LABEL

LONG LASTING FOR EPIC FRESHNESS

TheraBreath™

HEALTHY GUMS

DENTIST FORMULATED TOOTHPASTE

Anticavity/Antigingivitis

REDUCES GUMLINE PLAQUE FOR 24 HOURS*

TWIN PACK *in a clinical study with twice daily brushing vs a regular toothpaste

Neutralizes the source of bad breatht

tin laboratory tests

Gently whitens

Dr. Harold Katz

Clean Mint

2 TUBES of 4.0 oz (113 g)

TOTAL NET WT. 8.0 oz (226 g)